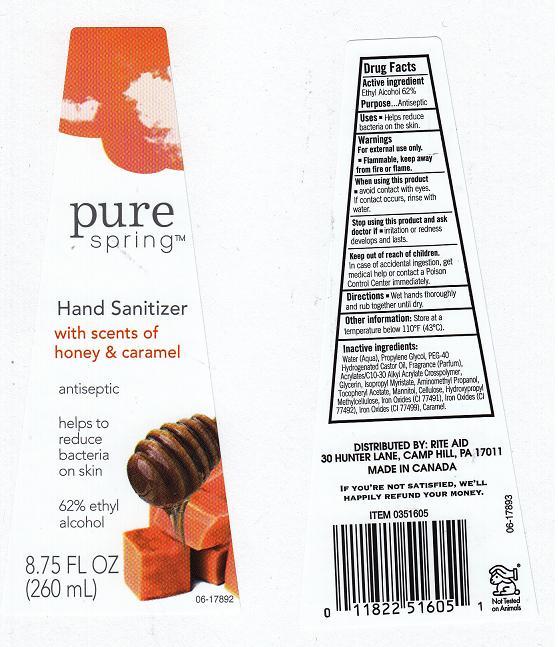 DRUG LABEL: PURE SPRING
NDC: 11822-4650 | Form: LIQUID
Manufacturer: RITE AID
Category: otc | Type: HUMAN OTC DRUG LABEL
Date: 20120305

ACTIVE INGREDIENTS: ALCOHOL 62 mL/100 mL
INACTIVE INGREDIENTS: WATER; PROPYLENE GLYCOL; POLYOXYL 40 HYDROGENATED CASTOR OIL; CARBOMER 934; GLYCERIN; ISOPROPYL MYRISTATE; AMINOMETHYLPROPANOL; ALPHA-TOCOPHEROL ACETATE; MANNITOL; ALPHA CELLULOSE; HYPROMELLOSE 2208 (4000 MPA.S); FERRIC OXIDE RED; FERRIC OXIDE YELLOW; FERROSOFERRIC OXIDE; CARAMEL

DRUG FACTS

ACTIVE INGREDIENT

ETHYL ALCOHOL 62%

PURPOSE

ANTISEPTIC

USES

HELPS REDUCE BACTERIA ON THE SKIN.

WARNINGS

FOR EXTERNAL USE ONLY. FLAMMABLE, KEEP AWAY FROM FIRE OR FLAME.

WHEN USING THIS PRODUCT

AVOID CONTACT WITH EYES. IF CONTACT OCCURS, RINSE WITH WATER.

STOP USING THIS PRODUCT AND ASK DOCTOR IF

IRRITATION OR REDNESS DEVELOPS AND LASTS.

KEEP OUT OF REACH OF CHILDREN

IN CASE OF ACCIDENTAL INGESTION, GET MEDICAL HELP OR CONTACT A POISON CONTROL CENTER IMMEDIATELY.

DIRECTIONS

WET HANDS THOROUGHLY AND RUB TOGETHER UNTIL DRY.

OTHER INFORMATION

STORE AT A TEMPERATURE BELOW 110F (43C).

INACTIVE INGREDIENTS:

WATER (AQUA), PROPYLENE GLYCOL, PEG-40 HYDROGENATED CASTOR OIL, FRAGRANCE (PARFUM), ACRYLATES/C10-30 ALKYL ACRYLATE CROSSPOLYMER, GLYCERIN, ISOPROPYL MYRISTATE, AMINOMETHYL PROPANOL, TOCOPHERYL ACETATE, MANNITOL, CELLULOSE, HYDROXYPROPYL METHYLCELLULOSE, IRON OXIDES (CI 77491), IRON OXIDES (CI 77492), IRON OXIDES (CI 77499), CARAMEL.